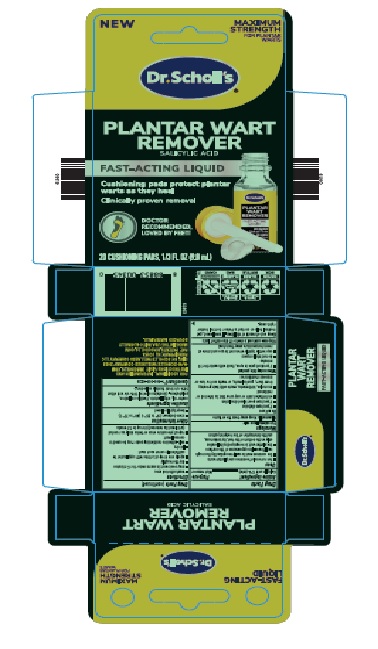 DRUG LABEL: Wart Remover
NDC: 73469-1192 | Form: LIQUID
Manufacturer: Scholls Wellness Company LLC
Category: otc | Type: HUMAN OTC DRUG LABEL
Date: 20231009

ACTIVE INGREDIENTS: SALICYLIC ACID 1.7 mg/10 mL
INACTIVE INGREDIENTS: CASTOR OIL; ETHYL LACTATE; CAMPHOR (SYNTHETIC); ETHER; ALCOHOL; POLYBUTENE (1400 MW)

90000412 Plantar Wart Remover liquid

Active ingredient

Salicylic acid 17% (w/w)

Purpose

Wart remover

INDICATIONS AND USAGE

- for removal of common and plantar warts
- the common wart is easily recognized by the rough cauliflower-like appearance of the surface
- the plantar wart is recognized by its location only on the bottom of the foot, its tenderness, and the interruption fo the footprint pattern.

WARNINGS

For external use only

Flammable: Keep away from fire or flame

DO NOT USE

- if you have diabetes
- if you have poor bood circulation
- on irritated skin or any area that is infected or reddened
- on moles, birthmarks, warts with hair growing from them, genital warts, or warts on the face or mucous membranes

WHEN USING

- if product gets in eyes, flush with water for 15 minutes
- do not inhale vapors
- cap bottle tightly when not in use and store at room temperature away from heat

Stop use and ask a doctor if discomfort lasts

Keep out of reach of children.

If swallowed, get medical help or contact a Poison Control Center right away

Directions

- wash affected area
- may soak wart in warm water for 5 minutes
- dry thoroughly
- apply one drop at a time with applicator to sufficiently cover each wart
- let dry
- sel-adhesive cushioning pads may be used to conceal wart
- repeat procedire once or twice daily as needed (until wart is removed) for up to 12 weeks

Other information

- store between 20° to 25°C (68° to 77°F)
- keep tightly closed

Inactive ingredients

castor oil, ethyl lactate, flexible collodion, polybutene (contains alcohol 18% v/v and ether 53% v/v from flexibe collodion).

QUESTIONS

Qustions?

1-866-360-3226